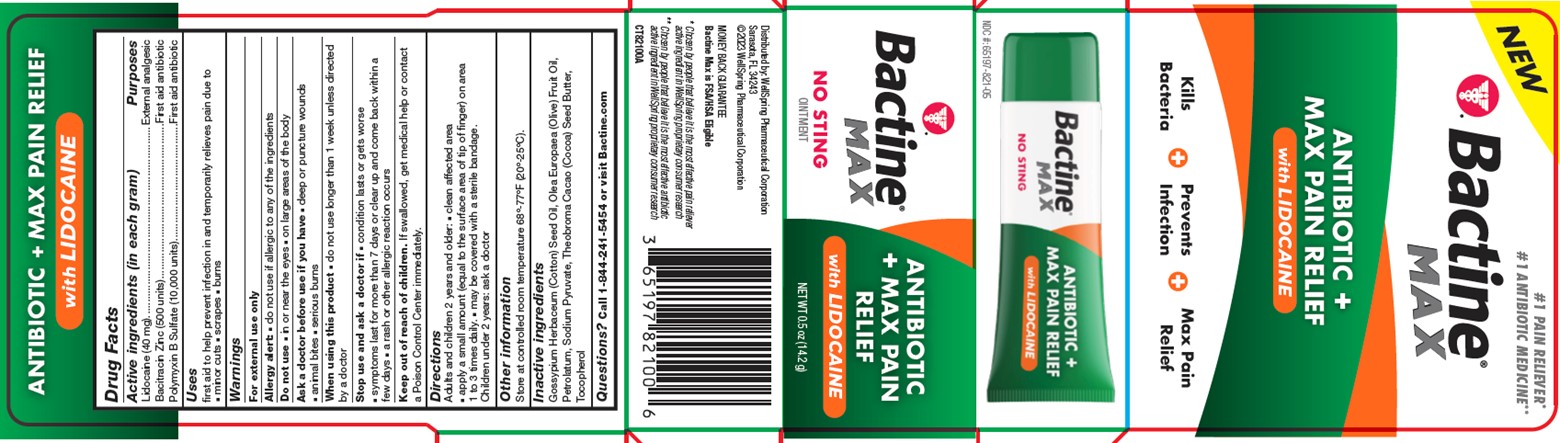 DRUG LABEL: Bactine Max Antibiotic and Lidocaine Max Pain Relief
NDC: 65197-827 | Form: OINTMENT
Manufacturer: WellSpring Pharmaceutical Corporation
Category: otc | Type: HUMAN OTC DRUG LABEL
Date: 20230608

ACTIVE INGREDIENTS: LIDOCAINE HYDROCHLORIDE 0.04 g/1 g; BACITRACIN ZINC 500 U/1 g; POLYMYXIN B SULFATE 10000 U/1 g
INACTIVE INGREDIENTS: PETROLATUM; OLEA EUROPAEA FRUIT VOLATILE OIL; GOSSYPIUM HERBACEUM SEED RESIN; SODIUM PYRUVATE; TOCOPHEROL; COCOA BUTTER

Bactine® Max Antibiotic and Lidocaine Max Pain Relief Ointment

Active Ingredients (w/w)

Lidocaine (40 mg)
Bacitracin Zinc (500 units)
Polymyxin B Sulfate (10,000 units)

Purpose

External analgesic
First aid antibiotic
First aid antibiotic

Uses

First aid to help prevent infection in and temporarily relieves pain due to

- minor cuts
- scrapes
- burns

Warnings

For external use only

Allergy alert

- do not use If you are allergic to any of the ingredients

Do not use

- in or near the eyes
- on large areas of the body

Ask a doctor before use if you have

- deep or puncture wounds
- animal bites
- serious burns

When using this product

- do not use longer than 1 week unless directed by a doctor

Stop use and ask a doctor if

- condition lasts or gets worse
- symptoms last for more than 7 days or clear up and come back within a few days
- a rash or other allergic reaction occurs

Keep out of reach of children

- If swallowed, get medical help or contact a Poison Control Center immediately.

Directions

Adults and children 2 years and older:

- clean affected area
- apply a small amount (equal to the surface area of tip of finger) on area 1 to 3 times daily.
- may be covered with a sterile bandage.

Children under 2 years: ask a doctor

Other information

Store at controlled room temperature 68º-77ºF (20º-25ºC).

Inactive ingredients

Gossypium Herbaceum (Cotton) Seed Oil, Olea Europaea (Olive) Fruit Oil, Petrolatum, Sodium Pyruvate, Theobroma Cacao (Cocoa) Seed Butter, Tocopherol

Questions?

Call 1-844-241-5454 or visit Bactine.com

Distributed by:

Distributed by: WellSpring Pharmaceutical Corporation
Sarasota, FL 34243
©2023 WellSpring Pharmaceutical Corporation

MONEY BACK GUARANTEE

Bactine Max is FSA/HSA Eligible

PACKAGE LABEL. PRINCIPAL DISPLAY PANEL

NDC #: 65197-827-05

NEW

#1 PAIN RELIEVER*

#1 ANTIBIOTIC MEDICINE**

ANTIBIOTIC + MAX PAIN RELIEF with LIDOCAINE

Kills Bacteria

Prevents Infection

Max Pain Relief

NET WT 0.5 oz (14.2 g)

NO STING - OINTMENT

*Chosen by people that believe it is the most effective pain reliever active ingredient in WellSpring proprietary consumer research

**Chosen by people that believe it is the most effective antibiotic active ingredient in WellSpring proprietary consumer research

CT82100A - Bactine Max Antibiotic